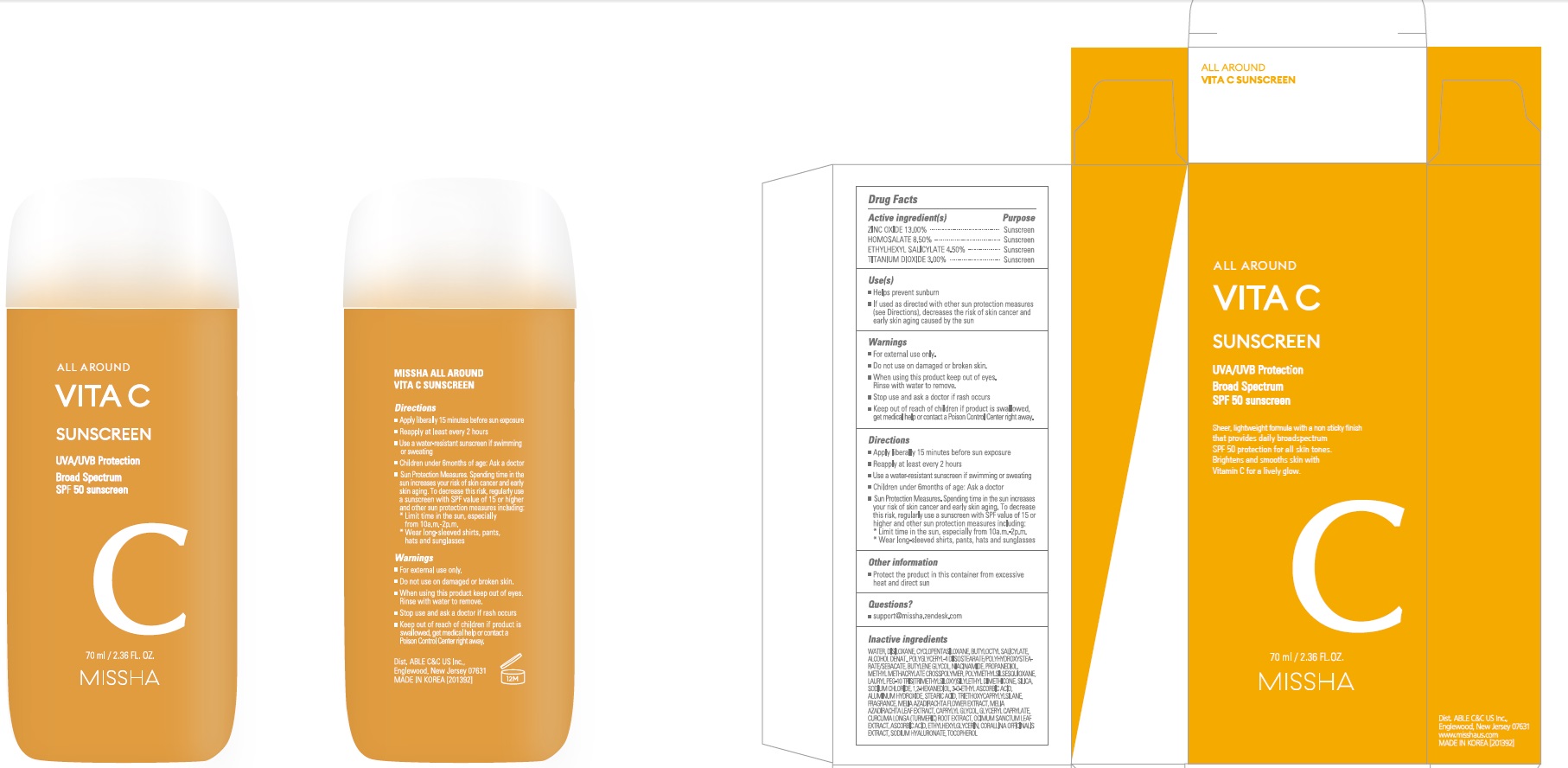 DRUG LABEL: MISSHA ALL AROUND VITA C SUNSCREEN
NDC: 13733-500 | Form: CREAM
Manufacturer: Able C&C Co., Ltd.
Category: otc | Type: HUMAN OTC DRUG LABEL
Date: 20241205

ACTIVE INGREDIENTS: OCTISALATE 4.5 g/100 mL; TITANIUM DIOXIDE 3 g/100 mL; HOMOSALATE 8.5 g/100 mL; ZINC OXIDE 13 g/100 mL
INACTIVE INGREDIENTS: WATER; HEXAMETHYLDISILOXANE; CYCLOMETHICONE 5

Active ingredient(s)

ZINC OXIDE 13.00%

HOMOSALATE 8.50%

ETHYLHEXYL SALICYLATE 4.50%

TITANIUM DIOXIDE 3.00%

Inactive Ingredients

WATER, DISILOXANE, CYCLOPENTASILOXANE, BUTYLOCTYL SALICYLATE, ALCOHOL DENAT., POLYGLYCERYL-4 DIISOSTEARATE/POLYHYDROXYSTEARATE/SEBACATE, BUTYLENE GLYCOL, NIACINAMIDE, PROPANEDIOL, METHYL METHACRYLATE CROSSPOLYMER, POLYMETHYLSILSESQUIOXANE, LAURYL PEG-10 TRIS(TRIMETHYLSILOXY)SILYLETHYL DIMETHICONE, SILICA, SODIUM CHLORIDE, 1,2-HEXANEDIOL, 3-O-ETHYL ASCORBIC ACID, ALUMINUM HYDROXIDE, STEARIC ACID, TRIETHOXYCAPRYLYLSILANE, FRAGRANCE, MELIA AZADIRACHTA FLOWER EXTRACT, MELIA AZADIRACHTA LEAF EXTRACT, CAPRYLYL GLYCOL, GLYCERYL CAPRYLATE, CURCUMA LONGA (TURMERIC) ROOT EXTRACT, OCIMUM SANCTUM LEAF EXTRACT, ASCORBIC ACID, ETHYLHEXYLGLYCERIN, CORALLINA OFFICINALIS EXTRACT, SODIUM HYALURONATE, TOCOPHEROL

Purpose

Sunscreen

Warnings

■ For external use only.

■ Do not use on damaged or broken skin.

■ When using this product keep out of eyes. Rinse with water to remove.

■ Stop use and ask a doctor if rash occurs

■ Keep out of reach of children if product is swallowed, get medical help or contact a Poison Control Center right away.

■ Keep out of reach of children if product is swallowed, get medical help or contact a Poison Control Center right away.

INDICATIONS AND USAGE

Use(s)

■ helps prevent sunburn

■ if used as directed with other sun protection measures(see Directions), decreases the risk of skin cancer and early skin aging caused by the sun

Directions

■ Apply liberally 15 minutes before sun exposure

■ Reapply at least every 2 hours

■ Use a water-resistant sunscreen if swimming or sweating

Sun Protection Measures. Spending time in the sun increases your risk of skin cancer and early skin againg. To decrease this risk, regularly use a sunscreen with SPF value of 15 or higher and other sun protection measures including:

■ Limit time in the sun, especially from 10a.m.-2p.m.

■ Wear long-sleeved shirts, pants, hats and sunglasses

Other Information

■ Protect the product in this container from excessive heat and direct sun

Questions?

support@missha.zendesk.com